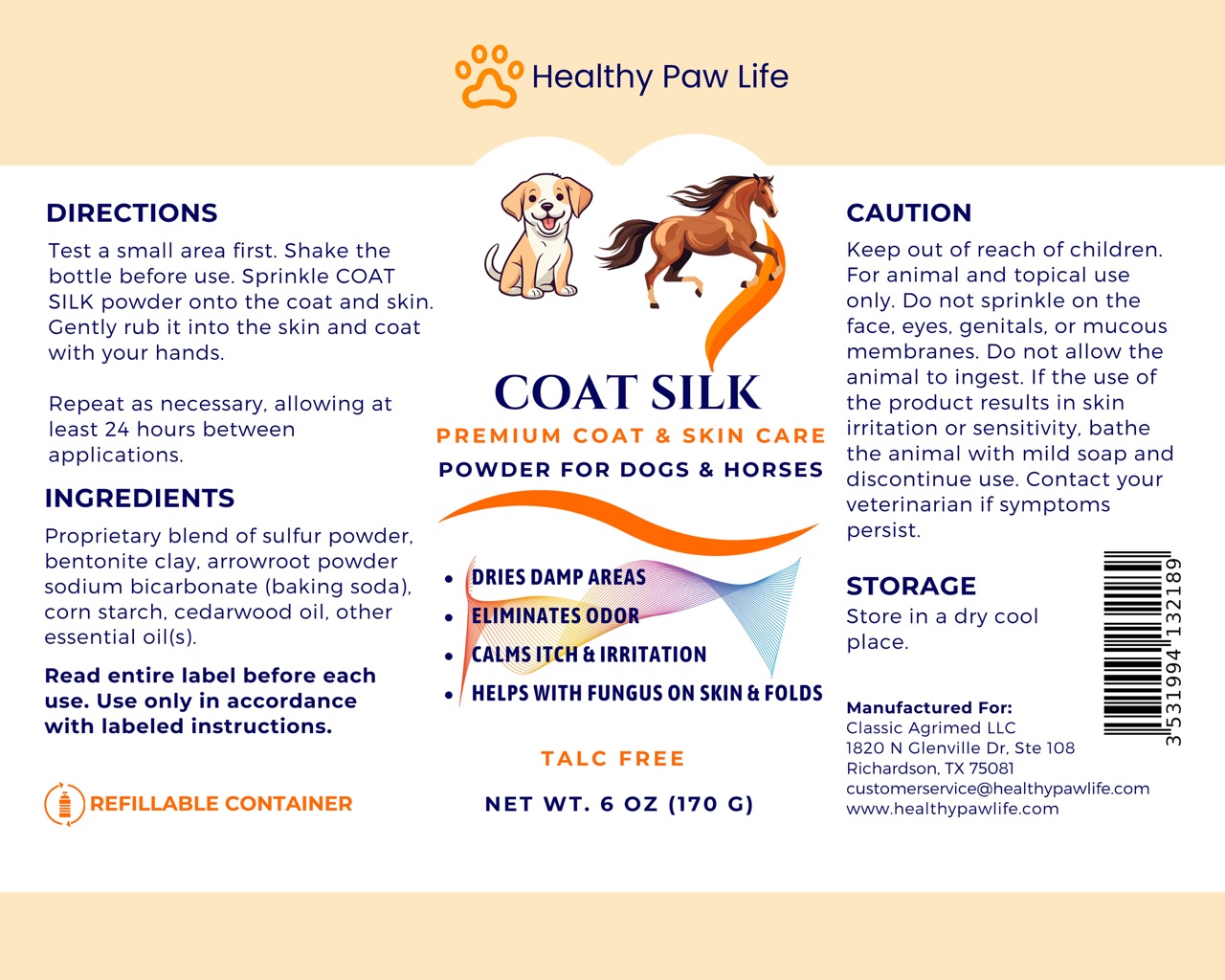 DRUG LABEL: HEALTHY PAW LIFE COAT SILK
NDC: 86130-904 | Form: POWDER
Manufacturer: CLASSIC AGRIMED LLC
Category: animal | Type: OTC ANIMAL DRUG LABEL
Date: 20240211

ACTIVE INGREDIENTS: SULFUR 5 g/100 g

HEALTHY PAW LIFE COAT SILK

Directions:

Test a small area first. Shake the bottle before use. Sprinkle COAT SILK powder onto the coat and skin. Gently rub it into the skin and coat with your hands.

Repeat as necessary, allowing at least 24 hours between applications.

Caution:

Keep out of reach of children. For animal and topical use only. Do not sprinkle on the face, eyes, genitals, or mucous membranes. Do not allow the animal to ingest. If the use of the product results in skin irritation or sensitivity, bathe the animal with mild soap and discontinue use. Contact your veterinarian if symptoms persist.

Ingredients:

Proprietary blend of sulfur powder, bentonite clay, arrowroot powder sodium bicarbonate (baking soda), corn starch, cedarwood oil, other essential oil(s).

Storage:

Store in a dry cool place.

Read entire label before each use. Use only in accordance with labeled instructions.